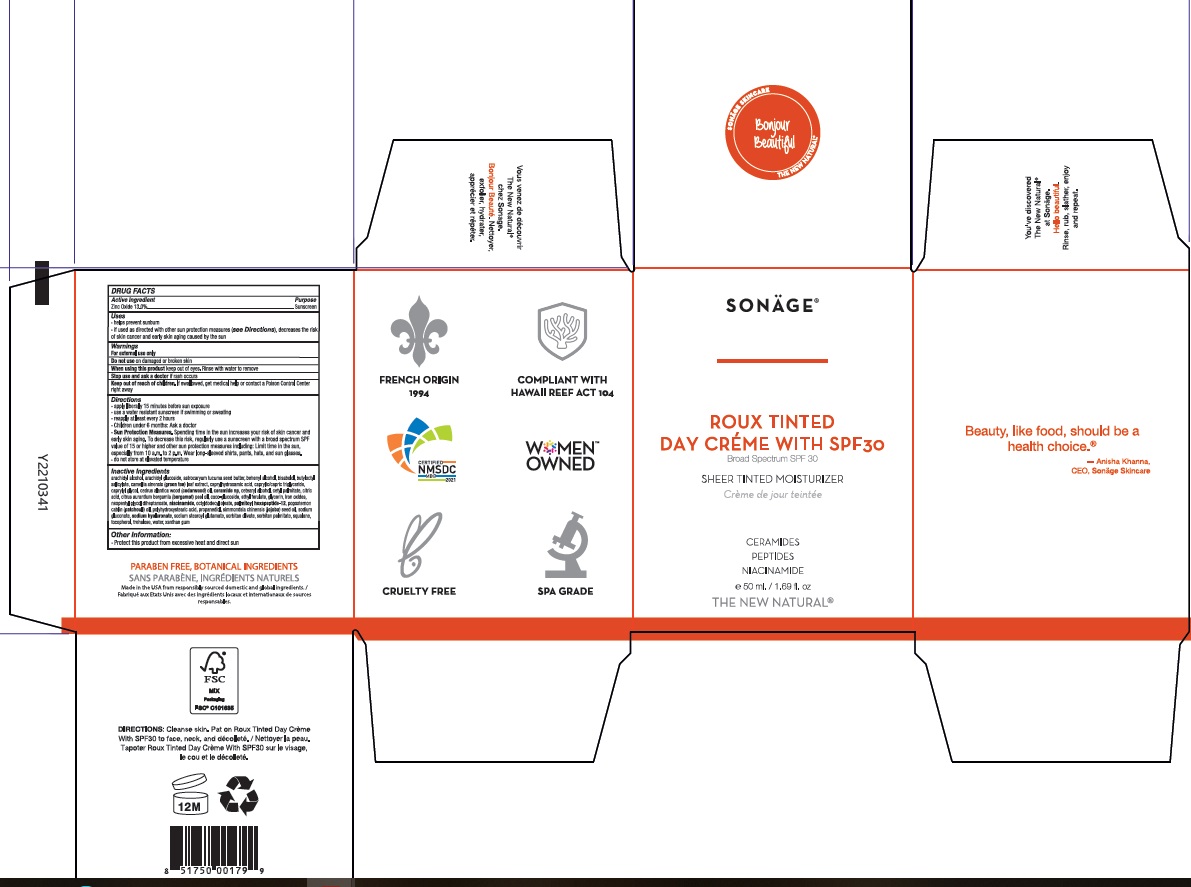 DRUG LABEL: Sonage Roux Tinted Day Creme with SPF 30
NDC: 69546-313 | Form: LOTION
Manufacturer: ASA Universal Inc. dba: Sonage
Category: otc | Type: HUMAN OTC DRUG LABEL
Date: 20241220

ACTIVE INGREDIENTS: ZINC OXIDE 13 g/100 mL
INACTIVE INGREDIENTS: TREHALOSE; SORBITAN MONOPALMITATE; GREEN TEA LEAF; CAPRYLHYDROXAMIC ACID; LEVOMENOL; CETOSTEARYL ALCOHOL; GLYCERIN; MEDIUM-CHAIN TRIGLYCERIDES; CETYL PALMITATE; CITRIC ACID MONOHYDRATE; COCO GLUCOSIDE; BERGAMOT OIL; POLYHYDROXYSTEARIC ACID (2300 MW); SODIUM GLUCONATE; HYALURONATE SODIUM; CAPRYLYL GLYCOL; PROPANEDIOL; SQUALANE; ALOE VERA LEAF; ARACHIDYL ALCOHOL; ARACHIDYL GLUCOSIDE; DOCOSANOL; BUTYLOCTYL SALICYLATE; XANTHAN GUM; WATER; SODIUM STEAROYL GLUTAMATE; TOCOPHEROL; NIACINAMIDE; CERAMIDE NP; ETHYL FERULATE; ASTROCARYUM ACULEATUM SEED OIL; PALMITOYL HEXAPEPTIDE-12; JOJOBA OIL; SORBITAN OLIVATE; FERRIC OXIDE YELLOW; FERRIC OXIDE RED; FERROSOFERRIC OXIDE; POGOSTEMON CABLIN LEAF OIL; CEDRUS ATLANTICA WOOD OIL; NEOPENTYL GLYCOL DIHEPTANOATE; OCTYLDODECYL OLEATE

Sonage - SPF 30 Roux Tinted Day Crème (15-EC-080)

ACTIVE INGREDIENT

Zinc Oxide - 13.0%

PURPOSE

Sunscreen

Uses

Helps prevent sunburn

If used as directed with other sun protection measures (see Directions), decreases the risk of skin cancer and early skin aging caused by the sun.

Warnings

For external use only.

Do not use on damaged or broken skin.

When using this product keep out of eyes. Rinse with water to remove.

Stop use and ask a doctor if rash occurs.

Keep out of reach of children. If swallowed, get medical help or contact a Poison Control Center right away.

Directions

Apply liberally 15 minutes before sun exposure.

Use a water resistant sunscreen if swimming or sweating

Rapply at least every 2 hours.

Children under 6 monts: Ask a doctor.

Sun Protection Measures. Spending time in the sun increases your risk of skin cancer and early skin aging. To decrease this risk, regularly use a sunscreen with a broad spectrum SPF value of 15 or higher and other sun protection measures including: Limit time in the sun, especially from 10 a.m. to 2 p.m. Wear long-sleeved shirts, pants, hats, and sun glasses.

Inactive Ingredients

Arachidyl Alcohol, Arachidyl Glucoside, Astrocaryum Tucuma Seed Butter, Behenyl Alcohol, Bisabolol, Butyloctyl Salicylate, Camellia Sinensis (Green Tea) Leaf Extract, Caprylhydroxamic Acid, Caprylic/Capric Triglyceride, Caprylyl Glycol, Cedrus Alantica Wood (Cedarwood) Oil, Ceramide NP, Cetearyl Alcohol, Cetyl Palmitate, Citric Acid, Citrus Aurantium Bergamia (Bergamot) Peel Oil, Coco-Glucoside, Ethyl Ferulate, Glycerin, Iron Oxides, Neopentyl Glycol Diheptanoate, Niacinamide, Octyldodecyl Oleate, Palmitoyl Hexapeptide-12, Pogostemon Cablin (Patchouli) Oil, Polyhydroxystearic Acid, Propanediol, Simmondsia Chinensis (Jojoba) Seed Oil, Sodium Gluconate, Sodium Hyaluronate, Sodium Stearoyl Glutamate, Sorbitan Olivate, Sorbitan Palmitate, Squalane, Tocopherol, Trehalose, Water, Xanthan Gum

Other Information

Protect this product from excessive heat and direct sun.